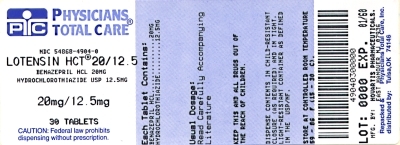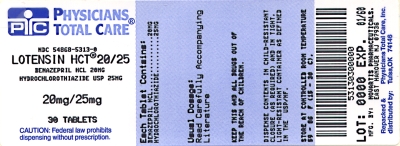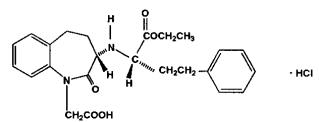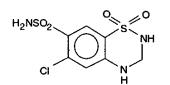 DRUG LABEL: Lotensin HCT
NDC: 54868-4904 | Form: TABLET
Manufacturer: Physicians Total Care, Inc.
Category: prescription | Type: HUMAN PRESCRIPTION DRUG LABEL
Date: 20120301

ACTIVE INGREDIENTS: BENAZEPRIL HYDROCHLORIDE 20 mg/1 1; HYDROCHLOROTHIAZIDE 12.5 mg/1 1
INACTIVE INGREDIENTS: CELLULOSE, MICROCRYSTALLINE; CROSPOVIDONE; HYDROGENATED CASTOR OIL; LACTOSE; POLYETHYLENE GLYCOLS; TALC; TITANIUM DIOXIDE

Lotensin HCT®

benazepril hydrochloride and hydrochlorothiazide USP

Combination Tablets

5 mg/6.25 mg
10 mg/12.5 mg
20 mg/12.5 mg
20 mg/25 mg

Rx only

Prescribing Information

WARNING: FETAL TOXICITY

When pregnancy is detected, discontinue Lotensin HCT as soon as possible.

Drugs that act directly on the renin-angiotensin system can cause injury and death to the developing fetus. See Warnings: Fetal Toxicity

DESCRIPTION

Benazepril hydrochloride is a white to off-white crystalline powder, soluble (>100 mg/mL) in water, in ethanol, and in methanol. Benazepril hydrochloride’s chemical name is 3-[[1-(ethoxycarbonyl)-3-phenyl-(1S)-propyl]amino]-2,3,4,5-tetrahydro-2-oxo-1H-1-(3S)-benzazepine-1-acetic acid monohydrochloride; its structural formula is

Its empirical formula is C24H28N2O5·HCl, and its molecular weight is 460.96.

Benazeprilat, the active metabolite of benazepril, is a nonsulfhydryl angiotensin-converting enzyme inhibitor. Benazepril is converted to benazeprilat by hepatic cleavage of the ester group.

Hydrochlorothiazide USP is a white, or practically white, practically odorless, crystalline powder. It is slightly soluble in water; freely soluble in sodium hydroxide solution, in n-butylamine, and in dimethylformamide; sparingly soluble in methanol; and insoluble in ether, in chloroform, and in dilute mineral acids. Hydrochlorothiazide’s chemical name is 6-chloro-3,4-dihydro-2H-1,2,4-benzothiadiazine-7-sulfonamide 1,1-dioxide; its structural formula is

Its empirical formula is C7 H8 ClN3 O4 S2, and its molecular weight is 297.73. Hydrochloro-thiazide is a thiazide diuretic.

Lotensin HCT is a combination of benazepril hydrochloride and hydrochlorothiazide USP. The tablets are formulated for oral administration with a combination of 5, 10, or 20 mg of benazepril hydrochloride and 6.25, 12.5, or 25 mg of hydrochlorothiazide USP. The inactive ingredients of the tablets are cellulose compounds, crospovidone, hydrogenated castor oil, iron oxides (10/12.5-mg, 20/12.5-mg, and 20/25-mg tablets), lactose, polyethylene glycol, talc, and titanium dioxide.

CLINICAL PHARMACOLOGY

Mechanism of Action

Benazepril and benazeprilat inhibit angiotensin-converting enzyme (ACE) in human subjects and in animals. ACE is a peptidyl dipeptidase that catalyzes the conversion of angiotensin I to the vasoconstrictor substance, angiotensin II. Angiotensin II also stimulates aldosterone secretion by the adrenal cortex.

Inhibition of ACE results in decreased plasma angiotensin II, which leads to decreased vasopressor activity and to decreased aldosterone secretion. The latter decrease may result in a small increase of serum potassium. Hypertensive patients treated with benazepril alone for up to 52 weeks had elevations of serum potassium of up to 0.2 mEq/L. Similar patients treated with benazepril and hydrochlorothiazide for up to 24 weeks had no consistent changes in their serum potassium (see PRECAUTIONS).

Removal of angiotensin II negative feedback on renin secretion leads to increased plasma renin activity. In animal studies, benazepril had no inhibitory effect on the vasopressor response to angiotensin II and did not interfere with the hemodynamic effects of the autonomic neurotransmitters acetylcholine, epinephrine, and norepinephrine.

ACE is identical to kininase, an enzyme that degrades bradykinin. Whether increased levels of bradykinin, a potent vasodepressor peptide, play a role in the therapeutic effects of Lotensin HCT remains to be elucidated.

While the mechanism through which benazepril lowers blood pressure is believed to be primarily suppression of the renin-angiotensin-aldosterone system, benazepril has an antihypertensive effect even in patients with low-renin hypertension.

Hydrochlorothiazide is a thiazide diuretic. Thiazides affect the renal tubular mechanisms of electrolyte reabsorption, directly increasing excretion of sodium and chloride in approximately equivalent amounts. Indirectly, the diuretic action of hydrochlorothiazide reduces plasma volume, with consequent increases in plasma renin activity, increases in aldosterone secretion, increases in urinary potassium loss, and decreases in serum potassium. The renin-aldosterone link is mediated by angiotensin, so coadministration of an ACE inhibitor tends to reverse the potassium loss associated with these diuretics.

The mechanism of the antihypertensive effect of thiazides is unknown.

Pharmacokinetics and Metabolism

Following oral administration of Lotensin HCT, peak plasma concentrations of benazepril are reached within 0.5-1.0 hours. As determined by urinary recovery, the extent of absorption is at least 37%. The absorption of hydrochlorothiazide is somewhat slower (1-2.5 hours) and somewhat more complete (50%-80%). In fasting subjects, the rate and extent of absorption of benazepril and hydrochlorothiazide from Lotensin HCT are not different, respectively, from the rate and extent of absorption of benazepril and hydrochlorothiazide from immediate-release monotherapy formulations.

The absorption of benazepril from Lotensin® tablets is not influenced by the presence of food in the gastrointestinal tract, but possible effects of food upon absorption of either component from Lotensin HCT tablets have not been studied. The reported studies of food effects on hydrochlorothiazide absorption have been inconclusive. The absorption of hydrochlorothiazide is increased by agents that reduce gastrointestinal motility, but it is reported to be reduced by 50% in patients with congestive heart failure.

Cleavage of the ester group (primarily in the liver) converts benazepril to its active metabolite, benazeprilat. Peak plasma concentrations of benazeprilat are reached 1-2 hours after drug intake in the fasting state and 2-4 hours after drug intake in the nonfasting state. The serum protein binding of benazepril is about 96.7% and that of benazeprilat about 95.3%, as measured by equilibrium dialysis; on the basis of in vitro studies, the degree of protein binding should be unaffected by age, hepatic dysfunction, or – over the concentration range of 0.24-23.6 µmol/L – concentration.

Hydrochlorothiazide is not metabolized. Its apparent volume of distribution is 3.6-7.8 L/kg, and its measured plasma protein binding is 67.9%. The drug also accumulates in red blood cells, so that whole blood levels are 1.6-1.8 times those measured in plasma.

In studies of rats given ^14C-benazepril, benazepril and its metabolites crossed the blood-brain barrier only to an extremely low extent. Multiple doses of benazepril did not result in accumulation in any tissue except the lung, where, as with other ACE inhibitors in similar studies, there was a slight increase in concentration due to slow elimination in that organ.

Some placental passage occurred when benazepril was administered to pregnant rats. In humans, hydrochlorothiazide crosses the placenta freely, and levels in umbilical-cord blood are similar to those in the maternal circulation.

Benazepril is almost completely metabolized to benazeprilat, which has much greater ACE inhibitory activity than benazepril, and to the glucuronide conjugates of benazepril and benazeprilat. Only trace amounts of an administered dose of benazepril can be recovered unchanged in the urine; about 20% of the dose is excreted as benazeprilat, 4% as benazepril glucuronide, and 8% as benazeprilat glucuronide.

In patients with hepatic dysfunction due to cirrhosis, levels of benazeprilat are essentially unaltered. Similarly, the pharmacokinetics of benazepril and benazeprilat do not appear to be influenced by age.

The kinetics of benazepril are dose-proportional within the dosage range of 5-20 mg. Small deviations from dose proportionality were observed when the broader range of 2-80 mg was studied, possibly due to the saturable binding of the compound to ACE.

The effective half-life of accumulation of benazeprilat following multiple dosing of benazepril hydrochloride is 10-11 hours. Thus, steady-state concentrations of benazeprilat should be reached after 2 or 3 doses of benazepril hydrochloride given once daily.

During chronic administration (28 days) of once-daily doses of benazepril between 5 mg and 20 mg, the kinetics did not change, and there was no significant accumulation. Accumulation ratios based on AUC and urinary recovery of benazeprilat were 1.19 and 1.27, respectively.

When dialysis was started 2 hours after ingestion of 10 mg of benazepril, approximately 6% of benazeprilat was removed in 4 hours of dialysis. The parent compound, benazepril, was not detected in the dialysate.

Benazepril and benazeprilat are cleared predominantly by renal excretion in healthy subjects with normal renal function. Nonrenal (i.e., biliary) excretion accounts for approximately 11%-12% of benazeprilat excretion in healthy subjects. In patients with renal failure, biliary clearance may compensate to an extent for deficient renal clearance.

The disposition of benazepril and benazeprilat in patients with mild-to-moderate renal insufficiency (creatinine clearance >30 mL/min) is similar to that in patients with normal renal function. In patients with creatinine clearance ≤30 mL/min, peak benazeprilat levels and the initial (alpha phase) half-life increase, and time to steady state may be delayed (see DOSAGE AND ADMINISTRATION).

Thiazide diuretics are eliminated by the kidney, with a terminal half-life of 5-15 hours. In a study of patients with impaired renal function (mean creatinine clearance of 19 mL/min), the half-life of hydrochlorothiazide elimination was lengthened to 21 hours.

Pharmacodynamics

Single and multiple doses of 10 mg or more of benazepril cause inhibition of plasma ACE activity by at least 80%-90% for at least 24 hours after dosing. For up to 4 hours after a 10-mg dose, pressor responses to exogenous angiotensin I were inhibited by 60%-90%.

Administration of benazepril to patients with mild-to-moderate hypertension results in a reduction of both supine and standing blood pressure to about the same extent, with no compensatory tachycardia. Symptomatic postural hypotension is infrequent, although it can occur in patients who are salt and/or volume depleted (see WARNINGS, Hypotension).

In single-dose studies, benazepril lowered blood pressure within 1 hour, with peak reductions achieved 2-4 hours after dosing. The antihypertensive effect of a single dose persisted for 24 hours. In multiple-dose studies, once-daily doses of 20-80 mg decreased seated pressure (systolic/diastolic) 24 hours after dosing by about 6-12/4-7 mmHg. The reductions at trough are about 50% of those seen at peak.

Four dose-response studies of benazepril monotherapy using once-daily dosing were conducted in 470 mild-to-moderate hypertensive patients not using diuretics. The minimal effective once-daily dose of benazepril was 10 mg; further falls in blood pressure, especially at morning trough, were seen with higher doses in the studied dosing range (10-80 mg). In studies comparing the same daily dose of benazepril given as a single morning dose or as a twice-daily dose, blood pressure reductions at the time of morning trough blood levels were greater with the divided regimen.

During chronic therapy with benazepril, the maximum reduction in blood pressure with any given dose is generally achieved after 1-2 weeks. The antihypertensive effects of benazepril have continued during therapy for at least 2 years. Abrupt withdrawal of benazepril has not been associated with a rapid increase in blood pressure.

In patients with mild-to-moderate hypertension, total daily doses of Lotensin 20-40 mg were similar in effectiveness to total daily doses of captopril 50-100 mg, hydrochlorothiazide 25-50 mg, nifedipine SR 40-80 mg, and propranolol 80-160 mg.

The antihypertensive effects of benazepril were not appreciably different in patients receiving high- or low-sodium diets.

In hemodynamic studies in dogs, blood pressure reduction was accompanied by a reduction in peripheral arterial resistance, with an increase in cardiac output and renal blood flow and little or no change in heart rate. In normal human volunteers, single doses of benazepril caused an increase in renal blood flow but had no effect on glomerular filtration rate.

In clinical trials of benazepril/hydrochlorothiazide using benazepril doses of 5-20 mg and hydrochlorothiazide doses of 6.25-25 mg, the antihypertensive effects were sustained for at least 24 hours, and they increased with increasing dose of either component. Although benazepril monotherapy is somewhat less effective in blacks than in nonblacks, the efficacy of combination therapy appears to be independent of race.

By blocking the renin-angiotensin-aldosterone axis, administration of benazepril tends to reduce the potassium loss associated with the diuretic. In clinical trials of Lotensin HCT, the average change in serum potassium was near zero in subjects who received 5/6.25 mg or 20/12.5 mg, but the average subject who received 10/12.5 mg or 20/25 mg experienced a mild reduction in serum potassium, similar to that experienced by the average subject receiving the same dose of hydrochlorothiazide monotherapy.

INDICATIONS AND USAGE

Lotensin HCT is indicated for the treatment of hypertension.

This fixed combination drug is not indicated for the initial therapy of hypertension (see DOSAGE AND ADMINISTRATION).

In using Lotensin HCT, consideration should be given to the fact that another angiotensin-converting enzyme inhibitor, captopril, has caused agranulocytosis, particularly in patients with renal impairment or collagen-vascular disease. Available data are insufficient to show that benazepril does not have a similar risk (see WARNINGS, Neutropenia/
Agranulocytosis).

Black patients receiving ACE inhibitors have been reported to have a higher incidence of angioedema compared to nonblacks.

CONTRAINDICATIONS

Lotensin HCT is contraindicated in patients who are anuric.

Lotensin HCT is also contraindicated in patients who are hypersensitive to benazepril, to any other ACE inhibitor, to hydrochlorothiazide, or to other sulfonamide-derived drugs. Hypersensitivity reactions are more likely to occur in patients with a history of allergy or bronchial asthma.

Lotensin HCT is also contraindicated in patients with a history of angioedema with or without previous ACE inhibitor treatment.

WARNINGS

Anaphylactoid and Possibly Related Reactions

Presumably because angiotensin-converting enzyme inhibitors affect the metabolism of eicosanoids and polypeptides, including endogenous bradykinin, patients receiving ACE inhibitors (including Lotensin HCT) may be subject to a variety of adverse reactions, some of them serious.

Head and Neck Angioedema: Angioedema of the face, extremities, lips, tongue, glottis, and larynx has been reported in patients treated with angiotensin-converting enzyme inhibitors. In U.S. clinical trials, symptoms consistent with angioedema were seen in none of the subjects who received placebo and in about 0.5% of the subjects who received benazepril. Angioedema associated with laryngeal edema can be fatal. If laryngeal stridor or angioedema of the face, tongue, or glottis occurs, treatment with Lotensin HCT should be discontinued and appropriate therapy instituted immediately. When involvement of the tongue, glottis, or larynx appears likely to cause airway obstruction, appropriate therapy, e.g., subcutaneous epinephrine injection 1:1000 (0.3-0.5 mL) should be promptly administered (see PRECAUTIONS and ADVERSE REACTIONS).

Intestinal Angioedema: Intestinal angioedema has been reported in patients treated with ACE inhibitors. These patients presented with abdominal pain (with or without nausea or vomiting); in some cases there was no prior history of facial angioedema and C-1 esterase levels were normal. The angioedema was diagnosed by procedures including abdominal CT scan or ultrasound, or at surgery, and symptoms resolved after stopping the ACE inhibitor. Intestinal angioedema should be included in the differential diagnosis of patients on ACE inhibitors presenting with abdominal pain.

Anaphylactoid Reactions During Desensitization: Two patients undergoing desensitizing treatment with hymenoptera venom while receiving ACE inhibitors sustained life-threatening anaphylactoid reactions. In the same patients, these reactions were avoided when ACE inhibitors were temporarily withheld, but they reappeared upon inadvertent rechallenge.

Anaphylactoid Reactions During Membrane Exposure: Anaphylactoid reactions have been reported in patients dialyzed with high-flux membranes and treated concomitantly with an ACE inhibitor. Anaphylactoid reactions have also been reported in patients undergoing low-density lipoprotein apheresis with dextran sulfate absorption.

Hypotension

Lotensin HCT can cause symptomatic hypotension. Like other ACE inhibitors, benazepril has been only rarely associated with hypotension in uncomplicated hypertensive patients. Symptomatic hypotension is most likely to occur in patients who have been volume and/or salt depleted as a result of prolonged diuretic therapy, dietary salt restriction, dialysis, diarrhea, or vomiting. Volume and/or salt depletion should be corrected before initiating therapy with Lotensin HCT.

Lotensin HCT should be used cautiously in patients receiving concomitant therapy with other antihypertensives. The thiazide component of Lotensin HCT may potentiate the action of other antihypertensive drugs, especially ganglionic or peripheral adrenergic-blocking drugs. The antihypertensive effects of the thiazide component may also be enhanced in the postsympathectomy patient.

In patients with congestive heart failure, with or without associated renal insufficiency, ACE inhibitor therapy may cause excessive hypotension, which may be associated with oliguria, azotemia, and (rarely) with acute renal failure and death. In such patients, Lotensin HCT therapy should be started under close medical supervision; they should be followed closely for the first 2 weeks of treatment and whenever the dose of benazepril or diuretic is increased.

If hypotension occurs, the patient should be placed in a supine position, and, if necessary, treated with intravenous infusion of physiological saline. Lotensin HCT treatment usually can be continued following restoration of blood pressure and volume.

Impaired Renal Function

Lotensin HCT should be used with caution in patients with severe renal disease. Thiazides may precipitate azotemia in such patients, and the effects of repeated dosing may be cumulative.

When the renin-angiotensin-aldosterone system is inhibited by benazepril, changes in renal function may be anticipated in susceptible individuals. In patients with severe congestive heart failure, whose renal function may depend on the activity of the renin-angiotensin-aldosterone system, treatment with angiotensin-converting enzyme inhibitors (including benazepril) may be associated with oliguria and/or progressive azotemia and (rarely) with acute renal failure and/or death.

In a small study of hypertensive patients with unilateral or bilateral renal artery stenosis, treatment with benazepril was associated with increases in blood urea nitrogen and serum creatinine; these increases were reversible upon discontinuation of benazepril therapy, concomitant diuretic therapy, or both. When such patients are treated with Lotensin HCT, renal function should be monitored during the first few weeks of therapy.

Some benazepril-treated hypertensive patients with no apparent preexisting renal vascular disease have developed increases in blood urea nitrogen and serum creatinine, usually minor and transient, especially when benazepril has been given concomitantly with a diuretic. Dosage reduction of Lotensin HCT may be required. Evaluation of the hypertensive patient should always include assessment of renal function (see DOSAGE AND ADMINISTRATION).

Neutropenia/Agranulocytosis

Another angiotensin-converting enzyme inhibitor, captopril, has been shown to cause agranulocytosis and bone marrow depression, rarely in uncomplicated patients (incidence probably less than once per 10,000 exposures) but more frequently (incidence possibly as great as once per 1000 exposures) in patients with renal impairment, especially those who also have collagen-vascular diseases such as systemic lupus erythematosus or scleroderma. Available data from clinical trials of benazepril are insufficient to show that benazepril does not cause agranulocytosis at similar rates. Monitoring of white blood cell counts should be considered in patients with collagen-vascular disease, especially if the disease is associated with impaired renal function.

Fetal Toxicity

Pregnancy Category D

Use of drugs that act on the renin-angiotensin system during the second and third trimesters of pregnancy reduces fetal renal function and increases fetal and neonatal morbidity and death. Resulting oligohydramnios can be associated with fetal lung hypoplasia and skeletal deformations. Potential neonatal adverse effects include skull hypoplasia, anuria, hypotension, renal failure, and death. When pregnancy is detected, discontinue Lotensin HCT as soon as possible. These adverse outcomes are usually associated with use of these drugs in the second and third trimester of pregnancy. Most epidemiologic studies examining fetal abnormalities after exposure to antihypertensive use in the first trimester have not distinguished drugs affecting the renin-angiotensin system from other antihypertensive agents. Appropriate management of maternal hypertension during pregnancy is important to optimize outcomes for both mother and fetus.

In the unusual case that there is no appropriate alternative to therapy with drugs affecting the renin-angiotensin system for a particular patient, apprise the mother of the potential risk to the fetus. Perform serial ultrasound examinations to assess the intra-amniotic environment. If oligohydramnios is observed, discontinue Lotensin HCT, unless it is considered lifesaving for the mother. Fetal testing may be appropriate, based on the week of pregnancy. Patients and physicians should be aware, however, that oligohydramnios may not appear until after the fetus has sustained irreversible injury. Closely observe infants with histories of in utero exposure to Lotensin HCT for hypotension, oliguria, and hyperkalemia [see Precautions, Pediatric Use].

No teratogenic effects of Lotensin were seen in studies of pregnant rats, mice, and rabbits. On a mg/m2 basis, the doses used in these studies were 60 times (in rats), 9 times (in mice), and more than 0.8 times (in rabbits) the maximum recommended human dose (assuming a 50-kg woman). On a mg/kg basis these these multiples are 300 times (in rats), 90 times (in mice), and more than 3 times (in rabbits) the maximum recommended human dose. When hydrochlorothiazide was orally administered without benazepril to pregnant mice and rats during their respective periods of major organogenesis, at doses up to 3000 and 1000 mg/kg/day respectively, there was no evidence of harm to the fetus. Similarly, no teratogenic effects of benazepril were seen in studies of pregnant rats, mice, and rabbits; on a mg/kg basis, the doses used in these studies were 300 times (in rats), 90 times (in mice), and more than 3 times (in rabbits) the maximum recommended human dose.

Hepatic Failure

Rarely, ACE inhibitors have been associated with a syndrome that starts with cholestatic jaundice and progresses to fulminant hepatic necrosis and (sometimes) death. The mechanism of this syndrome is not understood. Patients receiving ACE inhibitors who develop jaundice or marked elevations of hepatic enzymes should discontinue the ACE inhibitor and receive appropriate medical follow-up.

Impaired Hepatic Function

Lotensin HCT should be used with caution in patients with impaired hepatic function or progressive liver disease, since minor alterations of fluid and electrolyte balance may precipitate hepatic coma (see Hepatic Failure, above). In patients with hepatic dysfunction due to cirrhosis, levels of benazeprilat are essentially unaltered. No formal pharmacokinetic studies have been carried out in hypertensive patients with impaired liver function.

Systemic Lupus Erythematosus

Thiazide diuretics have been reported to cause exacerbation or activation of systemic lupus erythematosus.

Acute Myopia and Secondary Angle-Closure Glaucoma

Hydrochlorothiazide, a sulfonamide, can cause an idiosyncratic reaction, resulting in acute transient myopia and acute angle-closure glaucoma. Symptoms include acute onset of decreased visual acuity or ocular pain and typically occur within hours to weeks of drug initiation. Untreated acute angle-closure glaucoma can lead to permanent vision loss. The primary treatment is to discontinue hydrochlorothiazide as rapidly as possible. Prompt medical or surgical treatments may need to be considered if the intraocular pressure remains uncontrolled. Risk factors for developing acute angle-closure glaucoma may include a history of sulfonamide or penicillin allergy.

PRECAUTIONS

General

Derangements of Serum Electrolytes: In clinical trials of benazepril monotherapy, hyperkalemia (serum potassium at least 0.5 mEq/L greater than the upper limit of normal) occurred in approximately 1% of hypertensive patients receiving benazepril. In most cases, these were isolated values which resolved despite continued therapy. Risk factors for the development of hyperkalemia included renal insufficiency, diabetes mellitus, and the concomitant use of potassium-sparing diuretics, potassium supplements, and/or potassium-containing salt substitutes.

Conversely, treatment with thiazide diuretics has been associated with hypokalemia, hyponatremia, and hypochloremic alkalosis. These disturbances have sometimes been manifest as one or more of dryness of mouth, thirst, weakness, lethargy, drowsiness, restlessness, muscle pains or cramps, muscular fatigue, hypotension, oliguria, tachycardia, nausea, and vomiting. Hypokalemia can also sensitize or exaggerate the response of the heart to the toxic effects of digitalis. The risk of hypokalemia is greatest in patients with cirrhosis of the liver, in patients experiencing a brisk diuresis, in patients who are receiving inadequate oral intake of electrolytes, and in patients receiving concomitant therapy with corticosteroids or ACTH.

The opposite effects of benazepril and hydrochlorothiazide on serum potassium will approximately balance each other in many patients, so that no net effect upon serum potassium will be seen. In other patients, one or the other effect may be dominant. Initial and periodic determinations of serum electrolytes to detect possible electrolyte imbalance should be performed at appropriate intervals.

Chloride deficits are generally mild and require specific treatment only under extraordinary circumstances (e.g., in liver disease or renal disease). Dilutional hyponatremia may occur in edematous patients; appropriate therapy is water restriction rather than administration of salt, except in rare instances when the hyponatremia is life-threatening. In actual salt depletion, appropriate replacement is the therapy of choice.

Calcium excretion is decreased by thiazides. In a few patients on prolonged thiazide therapy, pathological changes in the parathyroid gland have been observed, with hypercalcemia and hypophosphatemia. More serious complications of hyperparathyroidism (renal lithiasis, bone resorption, and peptic ulceration) have not been seen.

Thiazides increase the urinary excretion of magnesium, and hypomagnesemia may result.

Other Metabolic Disturbances: Thiazide diuretics tend to reduce glucose tolerance and to raise serum levels of cholesterol, triglycerides, and uric acid. These effects are usually minor, but frank gout or overt diabetes may be precipitated in susceptible patients.

Cough: Presumably due to the inhibition of the degradation of endogenous bradykinin, persistent nonproductive cough has been reported with all ACE inhibitors, always resolving after discontinuation of therapy. ACE inhibitor-induced cough should be considered in the differential diagnosis of cough.

Surgery/Anesthesia: In patients undergoing surgery or during anesthesia with agents that produce hypotension, benazepril will block the angiotensin II formation that could otherwise occur secondary to compensatory renin release. Hypotension that occurs as a result of this mechanism can be corrected by volume expansion.

Information for Patients

Angioedema: Angioedema, including laryngeal edema, can occur at any time with treatment with ACE inhibitors. A patient receiving Lotensin HCT should be told to report immediately any signs or symptoms suggesting angioedema (swelling of face, eyes, lips, or tongue, or difficulty in breathing) and to take no more drug until after consulting with the prescribing physician.

Pregnancy: Female patients of childbearing age should be told about the consequences of exposure to Lotensin HCT during pregnancy. Discuss treatment options with women planning to become pregnant. Patients should be asked to report pregnancies to their physicians as soon as possible.

Symptomatic Hypotension: A patient receiving Lotensin HCT should be cautioned that lightheadedness can occur, especially during the first days of therapy, and that it should be reported to the prescribing physician. The patient should be told that if syncope occurs, Lotensin HCT should be discontinued until the physician has been consulted.

All patients should be cautioned that inadequate fluid intake, excessive perspiration, diarrhea, or vomiting can lead to an excessive fall in blood pressure, with the same consequences of lightheadedness and possible syncope.

Hyperkalemia: A patient receiving Lotensin HCT should be told not to use potassium supplements or salt substitutes containing potassium without consulting the prescribing physician.

Neutropenia: Patients should be told to promptly report any indication of infection (e.g., sore throat, fever), which could be a sign of neutropenia.

Laboratory Tests

The hydrochlorothiazide component of Lotensin HCT may decrease serum PBI levels without signs of thyroid disturbance.

Therapy with Lotensin HCT should be interrupted for a few days before carrying out tests of parathyroid function.

Drug Interactions

Potassium Supplements and Potassium-Sparing Diuretics: As noted above (Derangements of Serum Electrolytes), the net effect of Lotensin HCT may be to elevate a patient’s serum potassium, to reduce it, or to leave it unchanged. Potassium-sparing diuretics (spironolactone, amiloride, triamterene, and others) or potassium supplements can increase the risk of hyperkalemia. If concomitant use of such agents is indicated, they should be given with caution, and the patient’s serum potassium should be monitored frequently.

Lithium: Increased serum lithium levels and symptoms of lithium toxicity have been reported in patients receiving ACE inhibitors during therapy with lithium. Because renal clearance of lithium is reduced by thiazides, the risk of lithium toxicity is presumably raised further when, as in therapy with Lotensin HCT, a thiazide diuretic is coadministered with the ACE inhibitor. Lotensin HCT and lithium should be coadministered with caution, and frequent monitoring of serum lithium levels is recommended.

Gold: Nitritoid reactions (symptoms include facial flushing, nausea, vomiting and hypotension) have been reported rarely in patients on therapy with injectable gold (sodium aurothiomalate) and concomitant ACE inhibitor therapy.

Non-Steroidal Anti-Inflammatory Agents including Selective Cyclooxygenase-2 Inhibitors (COX-2 Inhibitors): In patients who are elderly, volume-depleted (including those on diuretic therapy), or with compromised renal function, co-administration of NSAIDs, including selective COX-2 inhibitors, with ACE inhibitors, including benazepril, may result in deterioration of renal function, including possible acute renal failure. These effects are usually reversible. Monitor renal function periodically in patients receiving benazepril and NSAID therapy.

The antihypertensive effect of ACE inhibitors and thiazide diuretics may be attenuated by NSAIDs. The diuretic and natriuretic effects of thiazide diuretics may also be reduced when NSAIDs are coadministered.

Other: Benazepril has been used concomitantly with beta-adrenergic-blocking agents, calcium-blocking agents, cimetidine, diuretics, digoxin, and hydralazine without evidence of clinically important adverse interactions. Other ACE inhibitors have had less than additive effects with beta-adrenergic blockers, presumably because drugs of both classes lower blood pressure by inhibiting parts of the renin-angiotensin system.

Interaction studies with warfarin and acenocoumarol have failed to identify any clinically important effects of benazepril on the serum concentrations or clinical effects of these anticoagulants.

Insulin requirements in diabetic patients may be increased, decreased, or unchanged.

Thiazides may decrease arterial responsiveness to norepinephrine, but not enough to preclude effectiveness of the pressor agent for therapeutic use.

Thiazides may increase the responsiveness to tubocurarine.

The diuretic, natriuretic, and antihypertensive effects of thiazide diuretics may be reduced by concurrent administration of nonsteroidal anti-inflammatory agents.

Cholestyramine and colestipol resins: Absorption of hydrochlorothiazide is impaired in the presence of anionic exchange resins. Single doses of either cholestyramine or colestipol resins bind the hydrochlorothiazide and reduce its absorption from the gastrointestinal tract by up to 85% and 43%, respectively.

Carcinogenesis, Mutagenesis, Impairment of Fertility

No evidence of carcinogenicity was found when benazepril was given to rats and mice for 104 weeks at doses up to 150 mg/kg/day. On a body-weight basis, this dose is over 100 times the maximum recommended human dose; on a body-surface-area basis, this dose is 18 times (rats) and 9 times (mice) the maximum recommended human dose. No mutagenic activity was detected in the Ames test in bacteria (with or without metabolic activation), in an in vitro test for forward mutations in cultured mammalian cells, or in a nucleus anomaly test. At doses of 50-500 mg/kg/day (38-375 times the maximum recommended human dose on a body-weight basis; 6-61 times the maximum recommended dose on a body-surface-area basis), benazepril had no adverse effect on the reproductive performance of male and female rats.

Under the auspices of the National Toxicology Program, rats and mice received hydrochlorothiazide in their feed for 2 years, at doses up to 600 mg/kg/day in mice and up to 100 mg/kg/day in rats. These studies uncovered no evidence of a carcinogenic potential of hydrochlorothiazide in rats or female mice, but there was equivocal evidence of hepatocarcinogenicity in male mice. Hydrochlorothiazide was not genotoxic in in vitro assays using strains TA 98, TA 100, TA 1535, TA 1537, and TA 1538 of Salmonella typhimurium (the Ames test); in the Chinese Hamster Ovary (CHO) test for chromosomal aberrations; or in in vivo assays using mouse germinal cell chromosomes, Chinese hamster bone marrow chromosomes, and the Drosophila sex-linked recessive lethal trait gene. Positive test results were obtained in the in vitro CHO Sister Chromatid Exchange (clastogenicity) test and in the Mouse Lymphoma Cell (mutagenicity) assays, using concentrations of hydrochlorothiazide of 43-1300 µg/mL. Positive test results were also obtained in the Aspergillus nidulans nondisjunction assay, using an unspecified concentration of hydrochlorothiazide.

Hydrochlorothiazide had no adverse effects on the fertility of mice and rats of either sex in studies wherein these species were exposed, via their diets, to doses up to 100 and 4 mg/kg/day, respectively, prior to mating and throughout gestation.

Nursing Mothers

Minimal amounts of unchanged benazepril and benazeprilat are excreted into the breast milk of lactating women treated with benazepril, so that a newborn child ingesting nothing but breast milk would receive less than 0.1% of the maternal doses of benazepril and benazeprilat. Thiazides, on the other hand, are definitely excreted into breast milk. Because of the potential for serious adverse reactions in nursing infants from hydrochlorothiazide and the unknown effects of benazepril in infants, a decision should be made whether to discontinue nursing or to discontinue Lotensin HCT, taking into account the importance of the drug to the mother.

Geriatric Use

Of the total number of patients who received Lotensin HCT in U.S. clinical studies of Lotensin HCT, 19% were 65 or older while about 1.5% were 75 or older. Overall differences in effectiveness or safety were not observed between these patients and younger patients, and other reported clinical experience has not identified differences in responses between the elderly and younger patients, but greater sensitivity of some older individuals cannot be ruled out.

Benazepril and benazeprilat are substantially excreted by the kidney. Because elderly patients are more likely to have decreased renal function, care should be taken in dose selection, and it may be useful to monitor renal function.

Pediatric Use

Neonates with a history of in utero exposure to Lotensin HCT:

If oliguria or hypotension occurs, direct attention toward support of blood pressure and renal perfusion. Exchange transfusions or dialysis may be required as a means of reversing hypotension and/or substituting for disordered renal function. Benazepril, which crosses the placenta, can theoretically be removed from the neonatal circulation by these means; there are occasional reports of benefit from these maneuvers with another ACE inhibitor, but experience is limited.

Safety and effectiveness in pediatric patients have not been established.

ADVERSE REACTIONS

Lotensin HCT has been evaluated for safety in over 2500 patients with hypertension; over 500 of these patients were treated for at least 6 months, and over 200 were treated for more than 1 year.

The reported side effects were generally mild and transient, and there was no relationship between side effects and age, sex, race, or duration of therapy. Discontinuation of therapy due to side effects was required in approximately 7% of U.S. patients treated with Lotensin HCT and in 4% of patients treated with placebo.

The most common reasons for discontinuation of therapy with Lotensin HCT in U.S. studies were cough (1.0%; see PRECAUTIONS), “dizziness” (1.0%), headache (0.6%), and fatigue (0.6%).

The side effects considered possibly or probably related to study drug that occurred in U.S. placebo-controlled trials in more than 1% of patients treated with Lotensin HCT are shown in the table below.

Reactions Possibly or Probably Drug Related
Patients in U.S. Placebo-Controlled Studies
 | LOTENSIN HCT N = 665 |  | Placebo N = 235
 | N | % | N | %
“Dizziness” | 41 | 6.3 | 8 | 3.4
Fatigue | 34 | 5.2 | 6 | 2.6
Postural Dizziness | 23 | 3.5 | 1 | 0.4
Headache | 20 | 3.1 | 10 | 4.3
Cough | 14 | 2.1 | 3 | 1.3
Hypertonia | 10 | 1.5 | 3 | 1.3
Vertigo | 10 | 1.5 | 2 | 0.9
Nausea | 9 | 1.4 | 2 | 0.9
Impotence | 8 | 1.2 | 0 | 0.0
Somnolence | 8 | 1.2 | 1 | 0.4

Other side effects considered possibly or probably related to study drug that occurred in U.S. placebo-controlled trials in 0.3% to 1.0% of patients treated with Lotensin HCT were the following:

Angioedema: Edema of the lips or face without other manifestations of angioedema (0.3%). See WARNINGS, Angioedema.

Cardiovascular: Hypotension (seen in 0.6% of patients), postural hypotension (0.3%), palpitations, and flushing.

Gastrointestinal: Vomiting, diarrhea, dyspepsia, anorexia, and constipation.

Neurologic and Psychiatric: Insomnia, nervousness, paresthesia, libido decrease, dry mouth, taste perversion, and tinnitus.

Dermatologic: Rash and sweating.

Other: Gout, urinary frequency, arthralgia, myalgia, asthenia, and pain (including chest pain and abdominal pain).

Other adverse experiences reported in 0.3% or more of Lotensin HCT patients in U.S. controlled clinical trials, and rarer events seen in post-marketing experience, were the following; asterisked entries occurred in more than 1% of patients (in some, a causal relationship to Lotensin HCT is uncertain):

Angioedema: Edema of the lips or face without other manifestations of angioedema. See WARNINGS, Angioedema.

Cardiovascular: Syncope, peripheral vascular disorder, and tachycardia.

Body as a Whole: Infection, back pain*, flu syndrome*, fever, chills, and neck pain.

Dermatologic: Photosensitivity and pruritus.

Gastrointestinal: Gastroenteritis, flatulence, and tooth disorder.

Neurologic and Psychiatric: Hypesthesia, abnormal vision, abnormal dreams, and retinal disorder.

Respiratory: Upper respiratory infection*, epistaxis, bronchitis, rhinitis*, sinusitis*, and voice alteration.

Other: Conjunctivitis, arthritis, urinary tract infection, alopecia, and urinary frequency*.

Monotherapy with benazepril has been evaluated for safety in over 6000 patients. In clinical trials, the observed adverse reactions to benazepril were similar to those seen in trials of Lotensin HCT. In post-marketing experience with benazepril, there have been rare reports of Stevens-Johnson syndrome, pancreatitis, hemolytic anemia, pemphigus, and thrombo-cytopenia. Another potentially important adverse experience, eosinophilic pneumonitis, has been attributed to other ACE inhibitors.

Hydrochlorothiazide has been extensively prescribed for many years, but there has not been enough systematic collection of data to support an estimate of the frequency of the observed adverse reactions. Within organ-system groups, the reported reactions are listed here in decreasing order of severity, without regard to frequency.

Unknown frequency: small bowel angioedema, anaphylactoid reactions, hyperkalemia, agranulocytosis, neutropenia.

Cardiovascular: Orthostatic hypotension (may be potentiated by alcohol, barbiturates, or narcotics).

Digestive: Pancreatitis, jaundice (intrahepatic cholestatic) (see WARNINGS), sialadenitis, vomiting, diarrhea, cramping, nausea, gastric irritation, constipation, and anorexia.

Neurologic: Vertigo, lightheadedness, transient blurred vision, headache, paresthesia, xanthopsia, weakness, and restlessness.

Musculoskeletal: Muscle spasm.

Hematologic: Aplastic anemia, agranulocytosis, leukopenia, and thrombocytopenia.

Metabolic: Hyperglycemia, glycosuria, and hyperuricemia.

Hypersensitivity: Necrotizing angiitis, respiratory distress (including pneumonitis and pulmonary edema), purpura, urticaria, rash, and photosensitivity.

Skin: Erythema multiforme including Stevens-Johnson syndrome, exfoliative dermatitis including toxic epidermal necrolysis.

Clinical Laboratory Test Findings

Serum Electrolytes: See PRECAUTIONS.

Creatinine: Minor reversible increases in serum creatinine were observed in patients with essential hypertension treated with Lotensin HCT. Such increases occurred most frequently in patients with renal artery stenosis (see PRECAUTIONS).

PBI and Tests of Parathyroid Function: See PRECAUTIONS.

Other (Causal Relationships Unknown): Other clinically important changes in standard laboratory tests were rarely associated with Lotensin HCT administration. Elevations in blood urea nitrogen, uric acid, glucose, SGOT, and SGPT have been reported (see WARNINGS). In the somewhat larger patient population exposed to benazepril monotherapy in U.S. trials, the same abnormalities were reported, together with scattered accounts of hyponatremia, melena, electrocardiographic changes, leukopenia, eosinophilia, and proteinuria.

OVERDOSAGE

No specific information is available on the treatment of overdosage with Lotensin HCT; treatment should be symptomatic and supportive. Therapy with Lotensin HCT should be discontinued, and the patient should be observed. Dehydration, electrolyte imbalance, and hypotension should be treated by established procedures.

Single oral doses of 1 g/kg of benazepril caused reduced activity in mice, and doses of 3 g/kg were associated with significant lethality. Reduction of activity in rats was not seen until they had received doses of 5 g/kg, and doses of 6 g/kg were not lethal. In single-dose studies of hydrochlorothiazide, most rats survived doses up to 2.75 g/kg.

Data from human overdoses of benazepril are scanty, but the most common manifestation of human benazepril overdosage is likely to be hypotension. In human hydrochlorothiazide overdose, the most common signs and symptoms observed have been those of dehydration and electrolyte depletion (hypokalemia, hypochloremia, hyponatremia). If digitalis has also been administered, hypokalemia may accentuate cardiac arrhythmias.

Laboratory determinations of serum levels of benazepril and its metabolites are not widely available, and such determinations have, in any event, no established role in the management of benazepril overdose.

No data are available to suggest physiological maneuvers (e.g., maneuvers to change the pH of the urine) that might accelerate elimination of benazepril and its metabolites. Benazeprilat is only slightly dialyzable, but dialysis might be considered in overdosed patients with severely impaired renal function (see WARNINGS).

Angiotensin II could presumably serve as a specific antagonist-antidote in the setting of benazepril overdose, but angiotensin II is essentially unavailable outside of scattered research facilities. Because the hypotensive effect of benazepril is achieved through vasodilation and effective hypovolemia, it is reasonable to treat benazepril overdose by infusion of normal saline solution.

DOSAGE AND ADMINISTRATION

Benazepril is an effective treatment of hypertension in once-daily doses of 10-80 mg, while hydrochlorothiazide is effective in doses of 12.5-50 mg per day. In clinical trials of benazepril/hydrochlorothiazide combination therapy using benazepril doses of 5-20 mg and hydrochlorothiazide doses of 6.25-25 mg, the antihypertensive effects increased with increasing dose of either component.

The side effects (see WARNINGS) of benazepril are generally rare and apparently independent of dose; those of hydrochlorothiazide are a mixture of dose-dependent phenomena (primarily hypokalemia) and dose-independent phenomena (e.g., pancreatitis), the former much more common than the latter. Therapy with any combination of benazepril and hydrochlorothiazide will be associated with both sets of dose-independent side effects, but regimens in which benazepril is combined with low doses of hydrochlorothiazide produce minimal effects on serum potassium. In clinical trials of Lotensin HCT, the average change in serum potassium was near zero in subjects who received 5/6.25 mg or 20/12.5 mg, but the average subject who received 10/12.5 mg or 20/25 mg experienced a mild reduction in serum potassium, similar to that experienced by the average subject receiving the same dose of hydrochlorothiazide monotherapy.

To minimize dose-independent side effects, it is usually appropriate to begin combination therapy only after a patient has failed to achieve the desired effect with monotherapy.

Dose Titration Guided by Clinical Effect: A patient whose blood pressure is not adequately controlled with benazepril monotherapy may be switched to Lotensin HCT 10/12.5 or Lotensin HCT 20/12.5. Further increases of either or both components could depend on clinical response. The hydrochlorothiazide dose should generally not be increased until 2-3 weeks have elapsed. Patients whose blood pressures are adequately controlled with 25 mg of daily hydrochlorothiazide, but who experience significant potassium loss with this regimen, may achieve similar blood-pressure control without electrolyte disturbance if they are switched to Lotensin HCT 5/6.25.

Replacement Therapy: The combination may be substituted for the titrated individual components.

Use in Renal Impairment: Regimens of therapy with Lotensin HCT need not take account of renal function as long as the patient’s creatinine clearance is >30 mL/min/1.73m^2 (serum creatinine roughly ≤3 mg/dL or 265 µmol/L). In patients with more severe renal impairment, loop diuretics are preferred to thiazides, so Lotensin HCT is not recommended (see WARNINGS).

HOW SUPPLIED

Lotensin HCT is available in tablets of four different strengths:

Benazepril | Hydrochlorothiazide | Tablet Color | Dose | Tablet Imprint | Bottle of | NDC Number
20 mg | 12.5 mg | grayish-violet | 20/12.5 | 74 | 10's | 54868-4904-1
 |  |  |  |  | 30's | 54868-4904-0
20 mg | 25 mg | red | 20/25 | 75 | 10's | 54868-5313-1
 |  |  |  |  | 30's | 54868-5313-0

Tablets are oblong and scored, with “Lotensin HCT” on one side and appropriate number imprinted on the other side.

Storage: Do not store above 30ºC (86ºF). Protect from moisture and light. Dispense in tight, light-resistant container (USP).

Manufactured by:

Novartis Pharmaceuticals Corporation

Suffern, New York 10901

Distributed by:

Novartis Pharmaceuticals Corporation

East Hanover, New Jersey 07936

© Novartis

T2012-46
January 2012

Relabeling and Repackaging by:
Physicians Total Care, Inc.
Tulsa, Oklahoma 74146

PRINCIPAL DISPLAY PANEL

Package Label

Rx Only

Lotensin HCT® 20/12.5

benazepril HCl 20 mg

hydrochlorothiazide USP 12.5 mg

PRINCIPAL DISPLAY PANEL

Package Label

Rx Only

Lotensin HCT® 20/25

benazepril HCl 20 mg

hydrochlorothiazide USP 25 mg